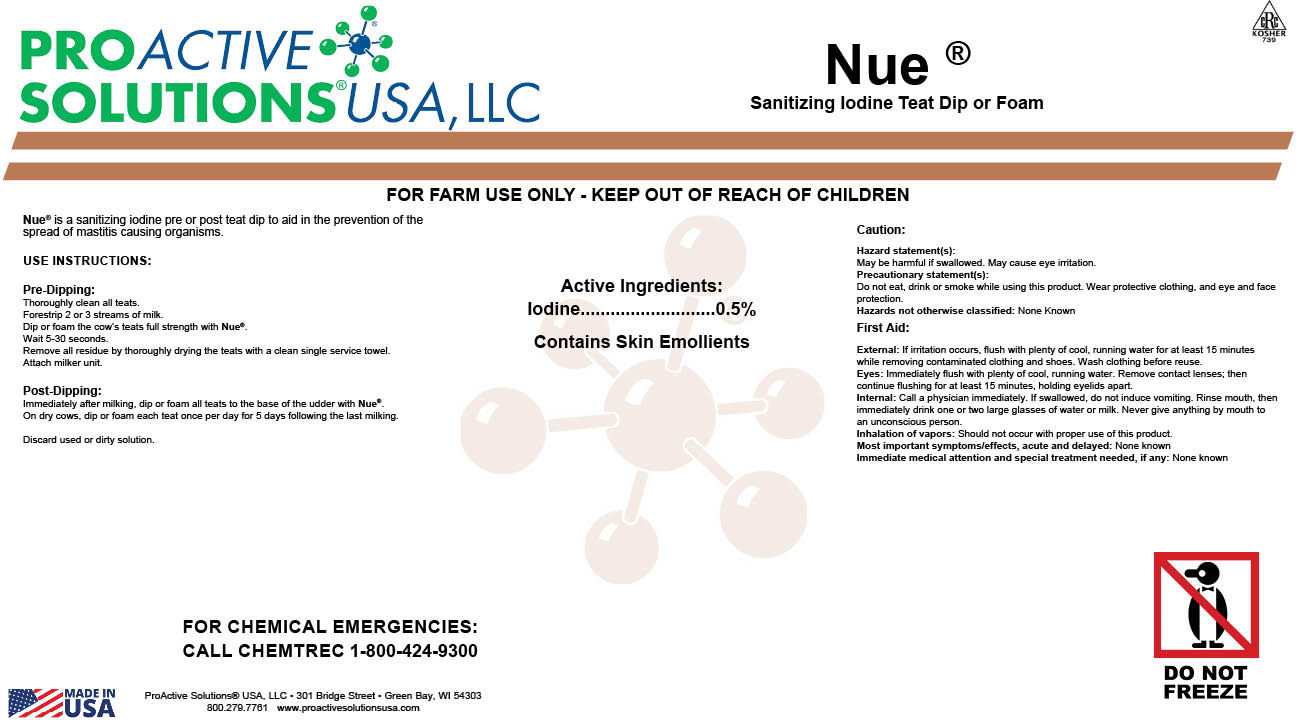 DRUG LABEL: Nue
NDC: 63927-4305 | Form: LIQUID
Manufacturer: ProActive Solutions USA, LLC
Category: animal | Type: OTC ANIMAL DRUG LABEL
Date: 20231220

ACTIVE INGREDIENTS: IODINE 0.5 kg/100 kg

Nue

Nue

Nue® is a sanitizing iodine pre or post teat dip to aid in the prevention of the spread of mastitis
causing organisms.

use instructions:

Pre-Dipping:
Thoroughly clean all teats.
Forestrip 2 or 3 streams of milk.
Dip or foam the cow’s teats full strength with Nue®.
Wait 5-30 seconds.
Remove all residue by thoroughly drying the teats with a clean single service towel.
Attach milker unit.

Post-Dipping:
Immediately after milking, dip or foam all teats to the base of the udder with Nue®.
On dry cows, dip or foam each teat once per day for 5 days following the last milking.

Discard used or dirty solution.

Caution:

Hazard statement(s):
May be harmful if swallowed. May cause eye irritation.
Precautionary statement(s):
Do not eat, drink or smoke while using this product. Wear protective clothing, and eye and
face protection.
Hazards not otherwise classified: None Known

First Aid:

External: If irritation occurs, flush with plenty of cool, running water for at least 15 minutes while removing contaminated clothing and shoes. Wash clothing before reuse.
Eyes: Immediately flush with plenty of cool, running water. Remove contact lenses; then
continue flushing for at least 15 minutes, holding eyelids apart.
Internal: Call a physician immediately. If swallowed, do not induce vomiting. Rinse mouth,
then immediately drink one or two large glasses of water or milk. Never give anything by
mouth to an unconscious person.
Inhalation of vapors: Should not occur with proper use of this product.
Most important symptoms/effects, acute and delayed: None known
Immediate medical attention and special treatment needed, if any: None known